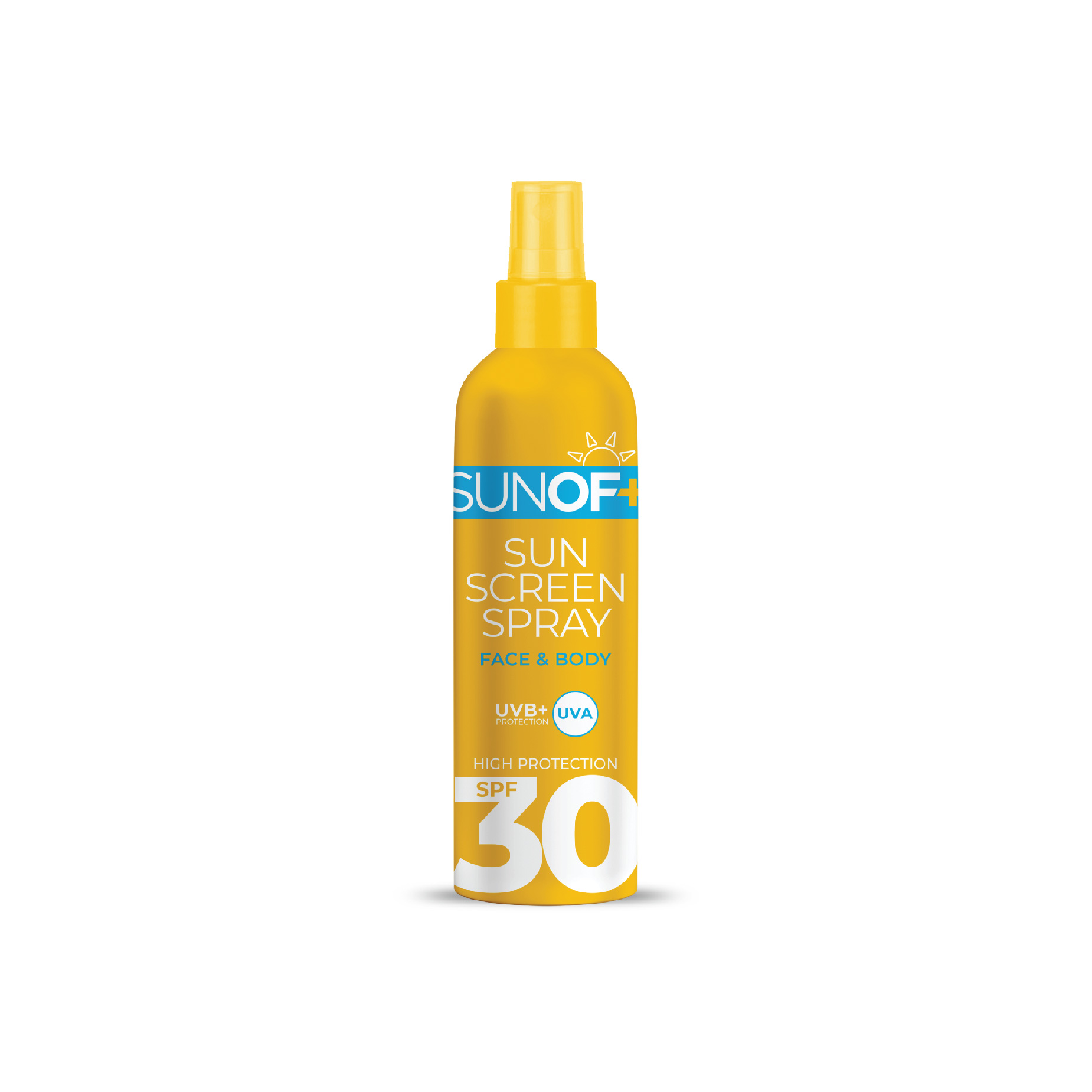 DRUG LABEL: SUNOF Sunscreen SPF 30
NDC: 77418-001 | Form: SPRAY
Manufacturer: ATAK FARMA KOZMETIK VE KIMYA SANAYI TICARET ANONIM SIRKETI
Category: otc | Type: HUMAN OTC DRUG LABEL
Date: 20250105

ACTIVE INGREDIENTS: OCTINOXATE 7.5 g/100 mL; AVOBENZONE 3 g/100 mL; OCTISALATE 5 g/100 mL
INACTIVE INGREDIENTS: CETEARYL ALCOHOL; ACRYLATES CROSSPOLYMER-4; PHENOXYETHANOL; SODIUM HYDROXIDE; ETHYLHEXYLGLYCERIN; PANTHENOL; ETHYLHEXYL STEARATE; GLYCERYL STEARATE; AQUA; ACRYLATES/METHOXY PEG-10 MALEATE/STYRENE COPOLYMER; PARFUMIDINE

INACTIVE INGREDIENT SECTION

Aqua , Ethylhexyl Stearate , Phenoxyethanol , Glyceryl Stearate , Acrylates Copolymer , Cetearyl Alcohol , Styrene/Acrylates Copolymer , Parfum , Ethylhexylglycerin ,Panthenol ,Tocopheryl Acetate.

WARNINGS

For external use only.

Do not use on damaged or broken skin.

When using this Product

Keep out of eyes.Rinse with water to remove.

Stop use and ask a doctor if rash occurs.

Keep out of reach of children. If Product is swallowed , get medical help or contact a Poison Control Center right away.

ACTIVE INGREDIENTS

Avobenzone 3.0%

Octisalate 5.0%

Octinoxate 7.5%

OTHER SAFETY INFORMATION

Protect this Product from excessive heat and direct sun

May stain some fabrics

Keep out reach of children

If Product is swallowed , get medical help or contact a Poison Control Center right away.

Directions

Apply generously 15 minutes before sun exposure. reapply : after 80 minutes of swimming or sweating.Immediately after towel drying. At least every 2 hours . Children under 6 months : Ask a doctor. Sun Protection Measures . Spending time in the sun increases your risk of skin cancer and early skin aging. To decrease this risk , regularly use a sunscreen with a board spectrum SPF value of 15 or higher and other sun protection measures including: limit time in the sun , especially from 10 a.m. – 2 p.m. wear long-sleeved shirts, pants,hats and sunglasses.